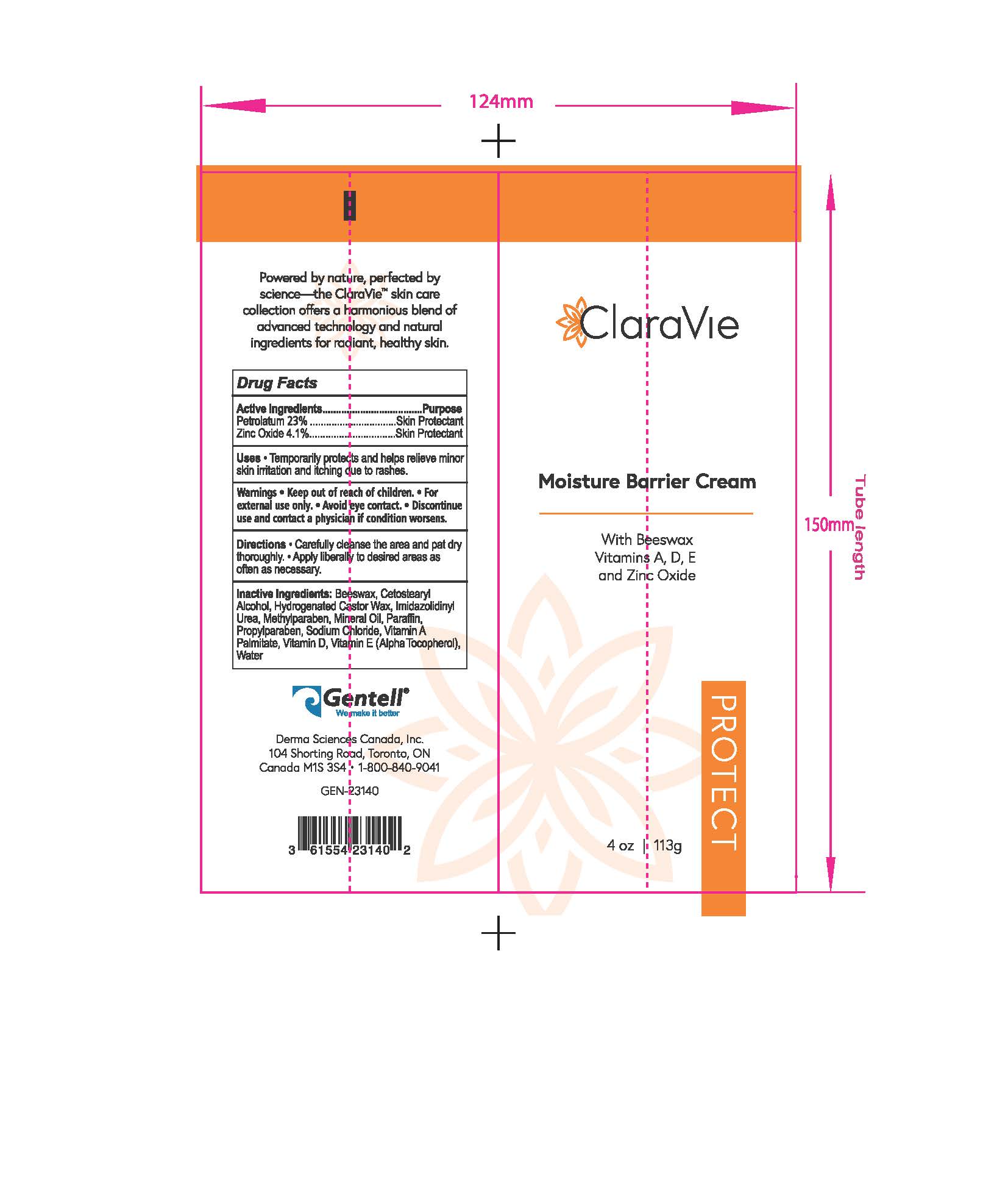 DRUG LABEL: Moisture Barrier Cream
NDC: 64772-204 | Form: CREAM
Manufacturer: Derma Sciences Canada Inc.
Category: otc | Type: HUMAN OTC DRUG LABEL
Date: 20251118

ACTIVE INGREDIENTS: PETROLATUM 0.23 g/1 g; ZINC OXIDE 0.041 g/1 g
INACTIVE INGREDIENTS: PROPYLPARABEN; PARAFFIN; .ALPHA.-TOCOPHEROL; WATER; HYDROGENATED CASTOR OIL; METHYLPARABEN; IMIDAZOLIDINYL UREA; VITAMIN A PALMITATE; VITAMIN D; SODIUM CHLORIDE; MINERAL OIL; BEESWAX; CETOSTEARYL ALCOHOL

Moisture Barrier Cream

ACTIVE INGREDIENT

Petrolatum 23%

Zinc Oxide 4.1 %

PURPOSE

Skin Protectant

Keep out of reach of children

INACTIVE INGREDIENT

Beeswax, Cetostearyl Alcohol, Hydrogenated Castor Wax, lmidazolidinyl Urea, Methylparaben, Mineral Oil, Paraffin, Propylparaben, Sodium Cl1Ioride, Vitamin A Palmitate, Vitamin D, Vitamin E (Alpha Tocopherol), Water

WARNINGS

Warnings • Keep out of reach of children • For external use only • Avoid eye contact. • Discontinue use and contact a physician if condition worsens

ASK DOCTOR

Discontinue use and contact a physician if condition worsens

INDICATIONS AND USAGE

Uses: Temporarily protects and helps relieve minor skin irritation and itching due to rashes.

DOSAGE AND ADMINISTRATION

Carefully cleanse the area and pat dry thoroughly. Apply liberally to desired areas often as necessary.

QUESTIONS

1-800-840-9041